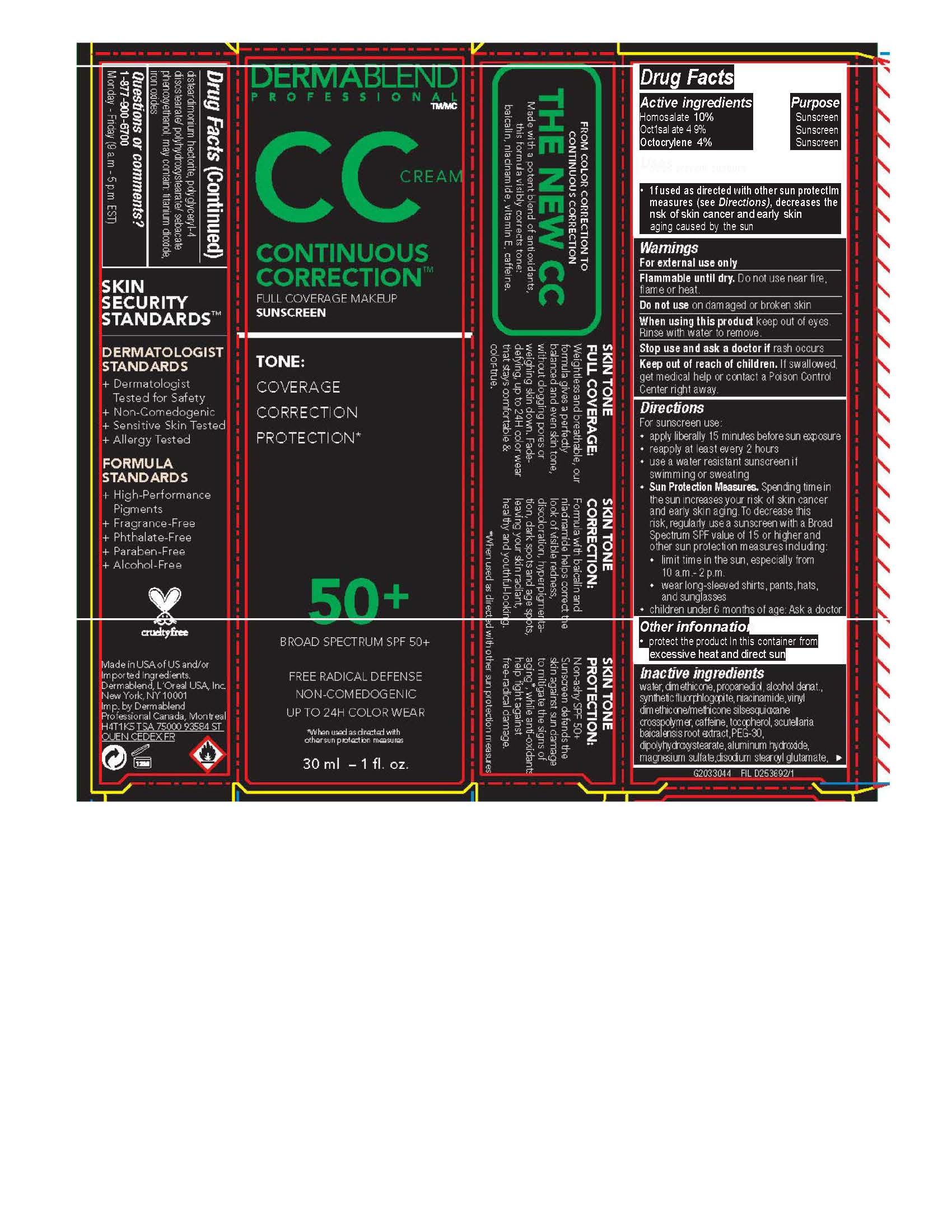 DRUG LABEL: Continuous Correction Cream
NDC: 84203-003 | Form: CREAM
Manufacturer: Baxter of California, LLC
Category: otc | Type: HUMAN OTC DRUG LABEL
Date: 20250724

ACTIVE INGREDIENTS: HOMOSALATE 100 mg/1 mL; OCTOCRYLENE 40 mg/1 mL; OCTISALATE 49 mg/1 mL
INACTIVE INGREDIENTS: MAGNESIUM POTASSIUM ALUMINOSILICATE FLUORIDE; TOCOPHEROL; SCUTELLARIA BAICALENSIS ROOT; PEG-30 DIPOLYHYDROXYSTEARATE; DISODIUM STEAROYL GLUTAMATE; FERRIC OXIDE RED; DISTEARDIMONIUM HECTORITE; MAGNESIUM SULFATE, UNSPECIFIED FORM; TITANIUM DIOXIDE; WATER; ALCOHOL; DIMETHICONE; PROPANEDIOL; NIACINAMIDE; CAFFEINE; PHENOXYETHANOL; ALUMINUM HYDROXIDE; VINYL DIMETHICONE/METHICONE SILSESQUIOXANE CROSSPOLYMER

Dermablend Professional CC Continuous Correction full coverage makeup broad spectrum SPF 50

Active ingredients

Homosalate 10% Octisalate 4.9% Octocrylene 4%

Purpose

Sunscreen

Uses

- helps prevent sunburn - if used as directed with other sun protection measures (see Directions), decreases the risk of skin cancer and early skin aging caused by the sun

Warnings

For external use only

Flammable until dry. Do not use near fire, flame or heat.

Do not use

on damaged or broken skin

When using this product

keep out of eyes. Rinse with water to remove.

Stop use and ask a doctor if

rash occurs

Keep out of reach of children.

If swallowed, get medical help or contact a Poison Control Center right away.

Directions

For sunscreen use: ● apply liberally 15 minutes before sun exposure ● reapply at least every 2 hours ● use a water resistant sunscreen if swimming or sweating ● Sun Protection Measures. Spending time in the sun increases your risk of skin cancer and early skin aging. To decrease this risk, regularly use a sunscreen with a Broad Spectrum SPF value of 15 or higher and other sun protection measures including: ● limit time in the sun, especially from 10 a.m. – 2 p.m. ● wear long-sleeved shirts, pants, hats, and sunglasses ● children under 6 months of age: Ask a doctor

Other information

protect the product in this container from excessive heat and direct sun

Inactive ingredients

water, dimethicone, propanediol, alcohol denat., synthetic fluorphlogopite, niacinamide, vinyl dimethicone/methicone silsesquioxane crosspolymer, caffeine, tocopherol, scutellaria baicalensis root extract, PEG-30 dipolyhydroxystearate, aluminum hydroxide, magnesium sulfate, disodium stearoyl glutamate, disteardimonium hectorite, polyglyceryl-4 diisostearate/polyhydroxystearate/sebacate, phenoxyethanol, may contain: titanium dioxide, iron oxides

Questions or comments?

1-877-900-6700 Monday - Friday (9 a.m. - 5 p.m. EST)